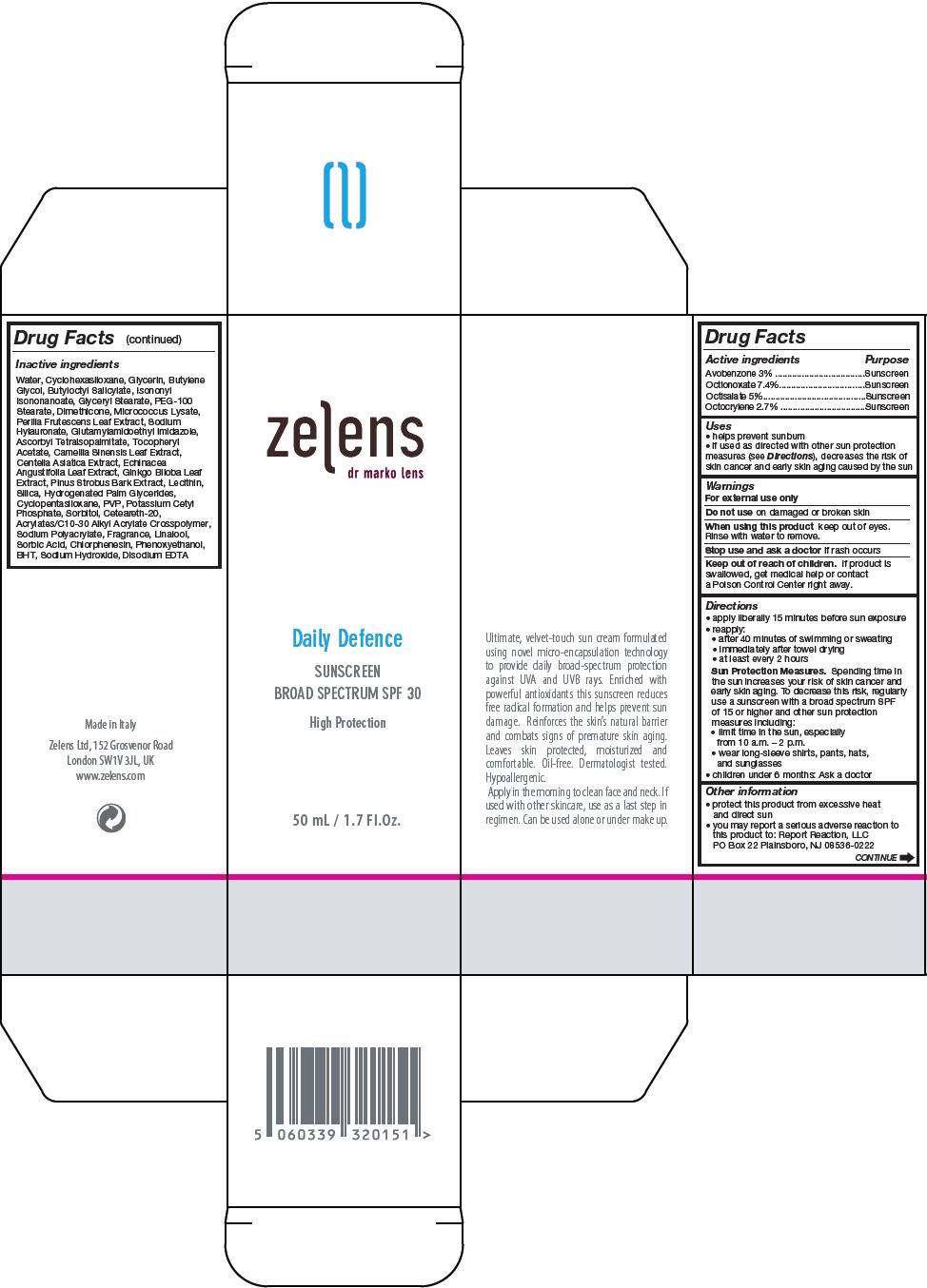 DRUG LABEL: DAILY DEFENCE SUNSCREEN Broad Spectrum SPF30
NDC: 63712-123 | Form: CREAM
Manufacturer: ZELENS Limited
Category: otc | Type: HUMAN OTC DRUG LABEL
Date: 20191106

ACTIVE INGREDIENTS: OCTINOXATE 74 mg/1 mL; OCTISALATE 50 mg/1 mL; AVOBENZONE 30 mg/1 mL; OCTOCRYLENE 27 mg/1 mL
INACTIVE INGREDIENTS: WATER; CYCLOMETHICONE 6; GLYCERIN; BUTYLENE GLYCOL; BUTYLOCTYL SALICYLATE; ISONONYL ISONONANOATE; GLYCERYL MONOSTEARATE; PEG-100 STEARATE; DIMETHICONE; PERILLA FRUTESCENS LEAF; HYALURONATE SODIUM; ASCORBYL TETRAISOPALMITATE; .ALPHA.-TOCOPHEROL ACETATE; GREEN TEA LEAF; CENTELLA ASIATICA; ECHINACEA ANGUSTIFOLIA LEAF; GINKGO; PINUS STROBUS BARK; SILICON DIOXIDE; HYDROGENATED PALM GLYCERIDES; CYCLOMETHICONE 5; POTASSIUM CETYL PHOSPHATE; SORBITOL; POLYOXYL 20 CETOSTEARYL ETHER; LINALOOL, (+/-)-; SORBIC ACID; CHLORPHENESIN; PHENOXYETHANOL; BUTYLATED HYDROXYTOLUENE; SODIUM HYDROXIDE; EDETATE DISODIUM

DAILY DEFENCE SUNSCREEN Broad Spectrum SPF30

Drug Facts

ACTIVE INGREDIENT

Active ingredients | Purpose
Avobenzone 3% | Sunscreen
Octionoxate 7.4% | Sunscreen
Octisalate 5% | Sunscreen
Octocrylene 2.7% | Sunscreen

Uses

- helps prevent sunburn
- if used as directed with other sun protection measures (see Directions), decreases the risk of skin cancer and early skin aging caused by the sun

Warnings

For external use only

Do not use on damaged or broken skin

When using this product keep out of eyes. Rinse with water to remove.

Stop use and ask a doctor if rash occurs

Keep out of reach of children. If product is swallowed, get medical help or contact a Poison Control Center right away.

Directions

- apply liberally 15 minutes before sun exposure
- reapply:
  - after 40 minutes of swimming or sweating
  - immediately after towel drying
  - at least every 2 hours
  Sun Protection Measures. Spending time in the sun increases your risk of skin cancer and early skin aging. To decrease this risk, regularly use a sunscreen with a broad spectrum SPF of 15 or higher and other sun protection measures including:
  - limit time in the sun, especially from 10 a.m. – 2 p.m.
  - wear long-sleeve shirts, pants, hats, and sunglasses
- children under 6 months: Ask a doctor

Other information

- protect this product from excessive heat and direct sun
- you may report a serious adverse reaction to this product to: Report Reaction, LLC PO Box 22 Plainsboro, NJ 08536-0222

Inactive ingredients

Water, Cyclohexasiloxane, Glycerin, Butylene Glycol, Butyloctyl Salicylate, Isononyl Isononanoate, Glyceryl Stearate, PEG-100 Stearate, Dimethicone, Micrococcus Lysate, Perilla Frutescens Leaf Extract, Sodium Hylauronate, Glutamylamidoethyl Imidazole, Ascorbyl Tetraisopalmitate, Tocopheryl Acetate, Camellia Sinensis Leaf Extract, Centella Asiatica Extract, Echinacea Angustifolia Leaf Extract, Ginkgo Biloba Leaf Extract, Pinus Strobus Bark Extract, Lecithin, Silica, Hydrogenated Palm Glycerides, Cyclopentasiloxane, PVP, Potassium Cetyl Phosphate, Sorbitol, Ceteareth-20, Acrylates/C10-30 Alkyl Acrylate Crosspolymer, Sodium Polyacrylate, Fragrance, Linalool, Sorbic Acid, Chlorphenesin, Phenoxyethanol, BHT, Sodium Hydroxide, Disodium EDTA

PRINCIPAL DISPLAY PANEL - 50 mL Tube Box

zelens
dr marko lens

Daily Defence

SUNSCREEN
BROAD SPECTRUM SPF 30

High Protection

50 mL / 1.7 Fl.Oz.